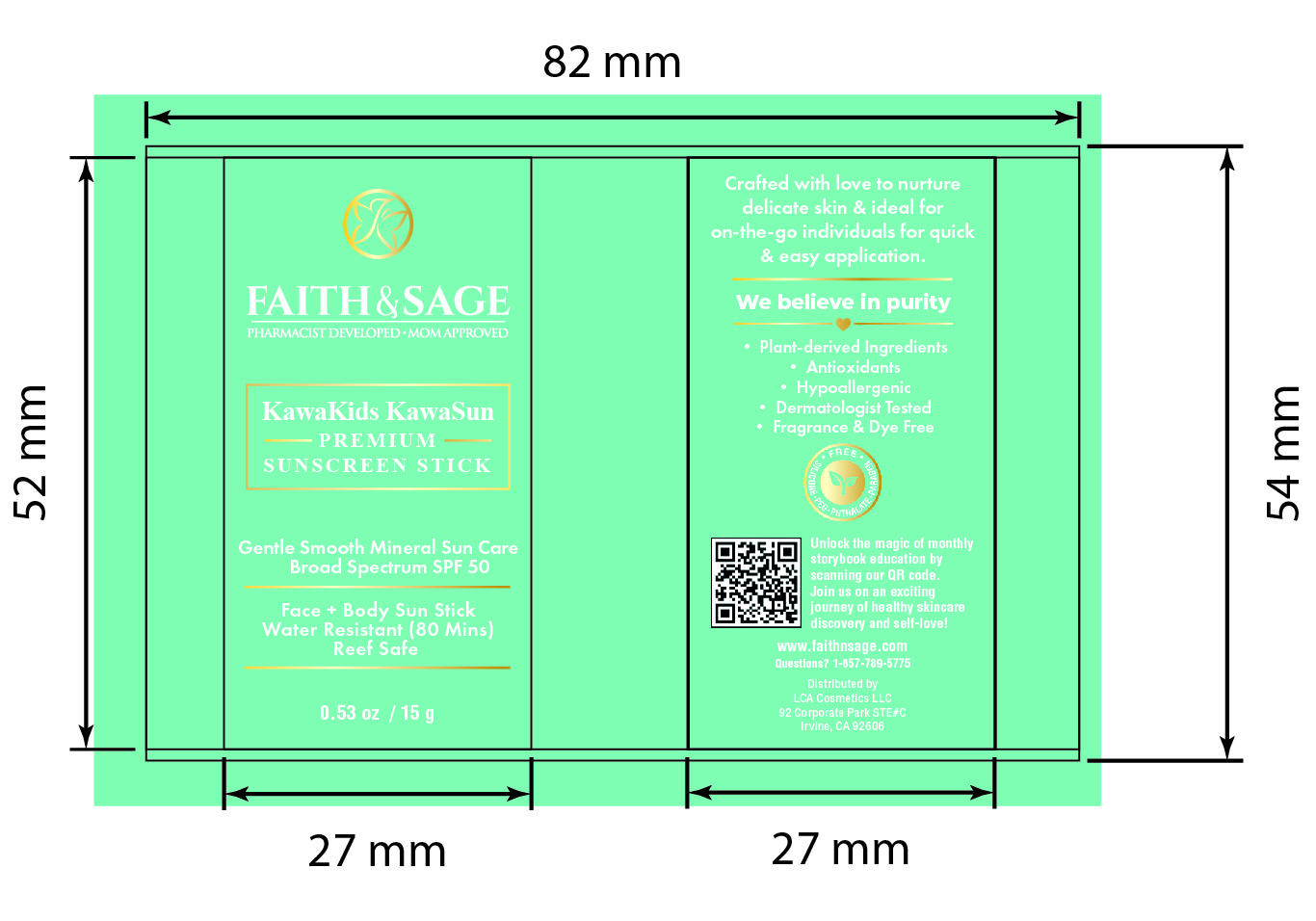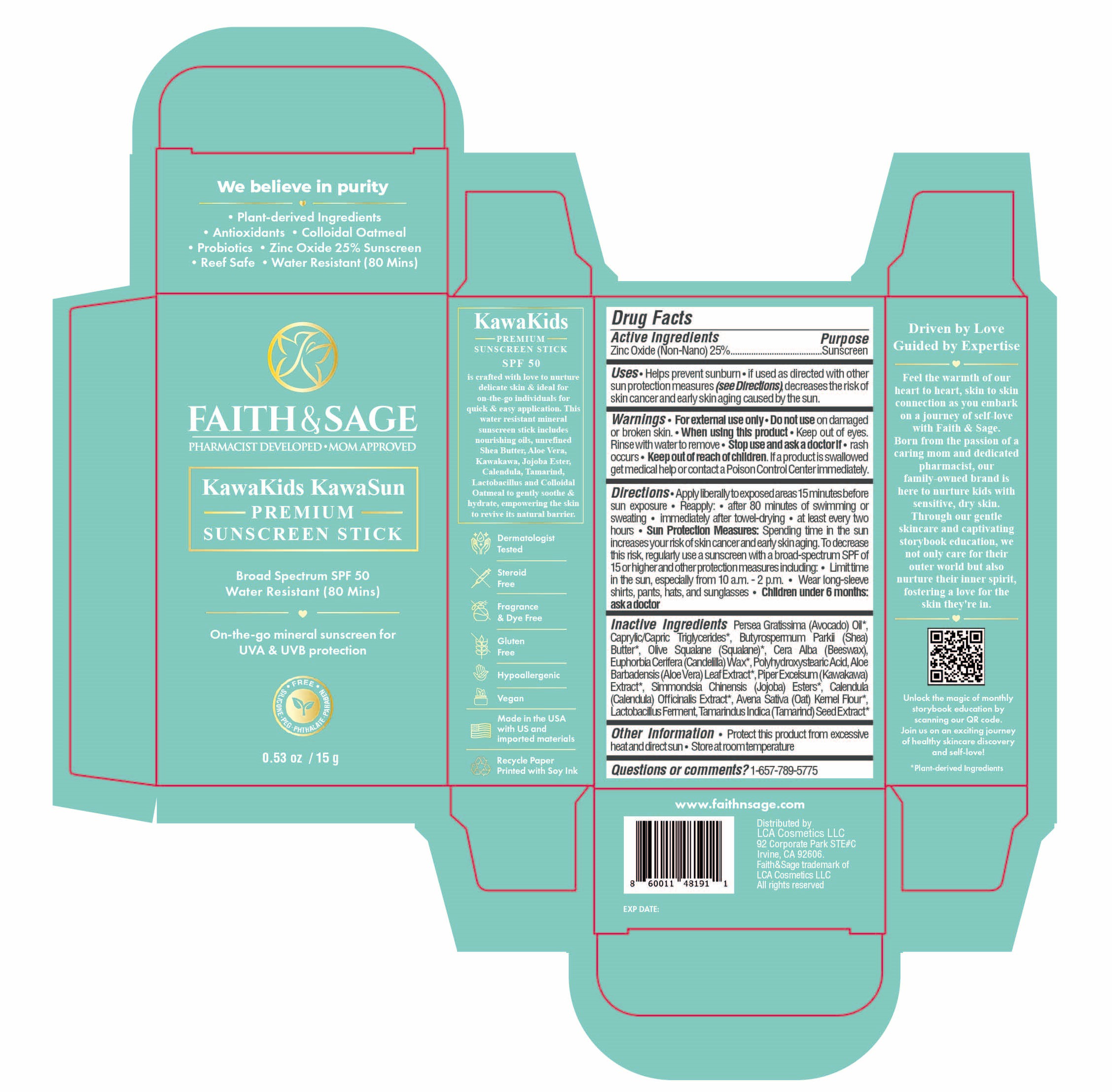 DRUG LABEL: KawaKids KawaSun - Premium On-The-Go Mineral Sunscreen SPF 50
NDC: 84569-911 | Form: STICK
Manufacturer: LCA COSMETICS LLC
Category: otc | Type: HUMAN OTC DRUG LABEL
Date: 20251212

ACTIVE INGREDIENTS: ZINC OXIDE 0.25 g/1 g
INACTIVE INGREDIENTS: SQUALANE; POLYHYDROXYSTEARIC ACID (2300 MW); AVOCADO OIL; MEDIUM-CHAIN TRIGLYCERIDES; BUTYROSPERMUM PARKII (SHEA) BUTTER UNSAPONIFIABLES; WHITE WAX; CANDELILLA WAX; ALOE VERA LEAF; PIPER EXCELSUM LEAF; JOJOBA OIL; CALENDULA OFFICINALIS FLOWER; OATMEAL; LIMOSILACTOBACILLUS FERMENTUM; TAMARIND SEED

KawaKids KawaSun - Premium On-The-Go Mineral Sunscreen SPF 50

Active ingredients

Zinc Oxide 25%

Purpose

Zinc Oxide 25%................Sunscreen

Uses

- Helps prevent sunburn
- If used as directed with other sun protection measures (see Directions) decreases the risk of skin cancer and early skin aging caused by the sun.

Warnings

For external use only

Do not useon damaged or broken skin.

When using this product

- Keep out of eyes. Rinse with water to remove.

Stop use and ask a doctor ifrash occurs.

Keep out of reach of children.If a product is swallowed get medical help or contact a Poison Control Center immediatley.

Directions

- Apply liberally to exposed areas 15 minutes before sun exposure
- Reapply:
- after 80 minutes of swimming or sweating
- immediately after towel drying
- at least every two hours
- Sun Protection Measures:Spending time in the sun increases your risk of skin cancer and early skin aging. To decrease this risk, regularly use a sunscreen with a broad spectrum SPF of 15 or higher and other protection measures including:
- Limit time in the sun, especially from 10am-2pm
- Wear long-sleeve shirts, pants, hats, and sunglasses
- Children under 6 months:ask a doctor

Inactive Ingredients

Persea Gratissima (Avocado) Oil, Caprylic/Capric Triglycerides, Butyrospermum Parkii (Shea) Butter, Olive Squalane (Suqalane), Cera Alba (Beeswax), Euphorbia Certifera (Candellia) Wax, Polyhydroxystearic Acid, Aloe Barbadensis (Aloe Vera) Leaf Extract, Piper Excelsum (Kawakawa) Extract, Simmondsia Chinensis (Jojoba) Esters, Calendula (Calendula) Officinalis Extract, Avena Sativa (Oat) Kernel Flour, Lactobacillus Ferment, Tamarindus Indica (Tamarind) Seed Extract

Other Information

- Protect this product from excessive heat and direct sun
- Store at room temperature

Questions or comments?

1-657-789-5775

PACKAGE LABEL

Faith & Sage

Pharmacist Developed

Mom Approved

KawaKids KawaSun

Premium

Sunscreen Stick

Broad Spectrum SPF 50

Water Resistant (80 Mins)

On-the-go mineral sunscreen for UVA & UVB Protection

Silicone PEG Phthalate Paraben Free

0.53 oz / 15 g